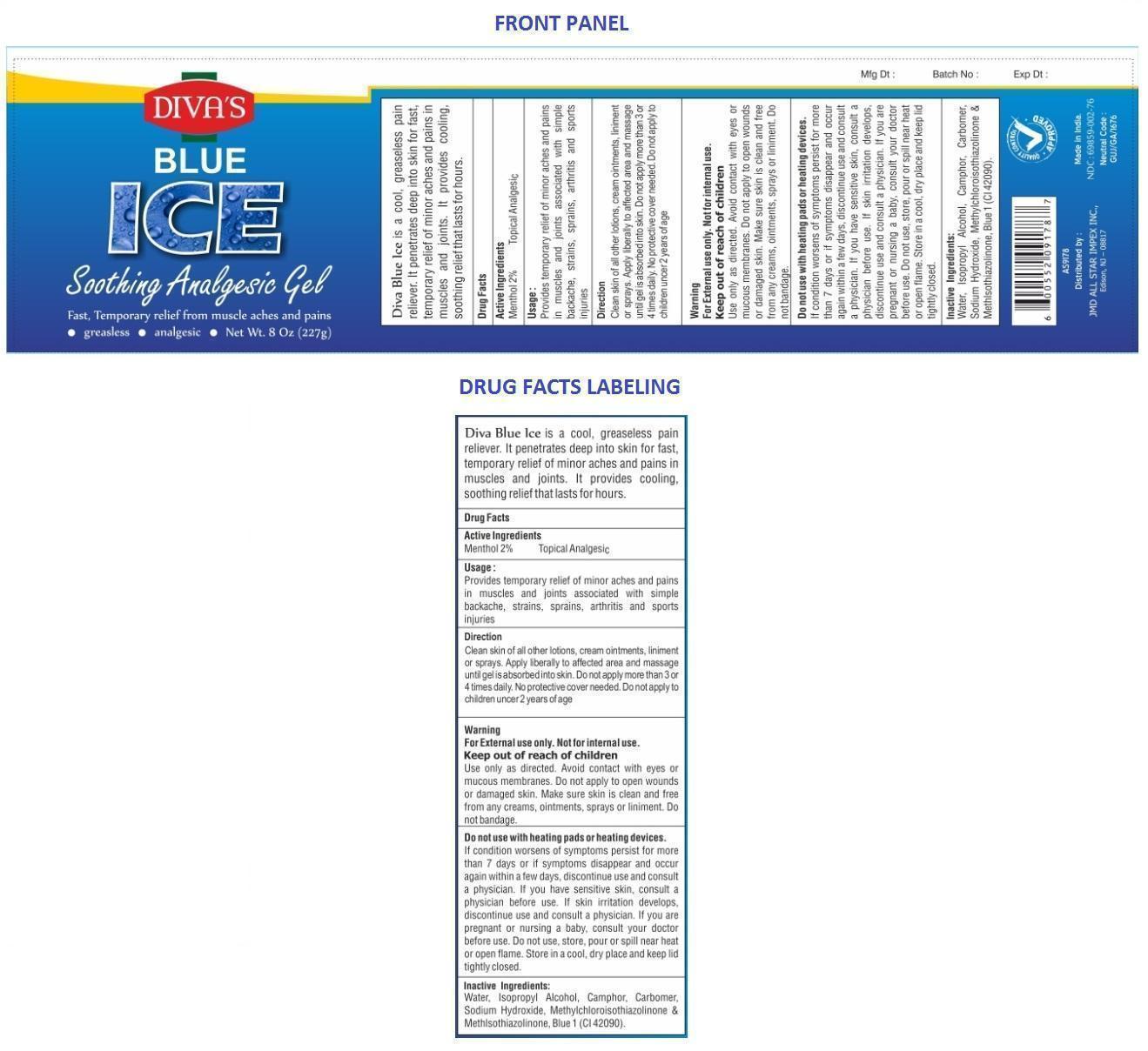 DRUG LABEL: BLUE ICE
NDC: 69859-002 | Form: GEL
Manufacturer: JT Cosmetics and Chemicals
Category: otc | Type: HUMAN OTC DRUG LABEL
Date: 20150601

ACTIVE INGREDIENTS: MENTHOL, UNSPECIFIED FORM 2 g/100 g
INACTIVE INGREDIENTS: WATER; ISOPROPYL ALCOHOL; CAMPHOR (NATURAL); CARBOMER HOMOPOLYMER TYPE C; SODIUM HYDROXIDE; METHYLCHLOROISOTHIAZOLINONE; METHYLISOTHIAZOLINONE; FD&C BLUE NO. 1

BLUE ICE

Diva Blue Ice is a cool, greaseless pain reliever. It penetrates deep into skin for fast, temporary relief of minor aches and pains in muscles and joints. It provides cooling, soothing relief that lasts for hours.

Active Ingredients

Menthol 2%

Purpose

Topical Analgesic

Keep out of reach of children.

Usage:

Provides temporary relief of minor aches and pains in muscles and joints associated with simple backache, strains, sprains, arthritis and sports injuries.

Warning

For External use only. Not for internal use.

Use only as directed. Avoid contact with eyes or mucous membranes. Do not apply to open wounds or damaged skin. Make sure skin is clean and free from any creams, ointments, sprays or liniment. Do not bandage.

Do not use with heating pads or heating devices.

If condition worsens of symptoms persist for more than 7 days or if symptoms disappear and occur again within a few days, discontinue use and consult a physician. If you have sensitive skin, consult a physician before use. If skin irritation develops, discontinue use and consult a physician. If you are pregnant or nursing a baby, consult your doctor before use.

Direction

Clean skin of all other lotions, cream ointments, liniment or sprays. Apply liberally to affected area and massage until gel is absorbed into skin. Do not apply more than 3 or 4 times daily. No protective cover needed. Do not apply to children under 2 years of age.

Inactive Ingredients:

Water, Isopropyl Alcohol, Camphor, Carbomer, Sodium Hydroxide, Methylchloroisothiazolinone & Methylisothiazolinone, Blue 1 (CI 42090).

Do not use, store, pour or spill near heat or open flame. Store in a cool, dry place and keep lid tightly closed.

Distributed by

JMD ALL STAR IMPEX INC.,

Edison, NJ - 08817

Made in India.

Neutral Code : GUJ/GA/1676